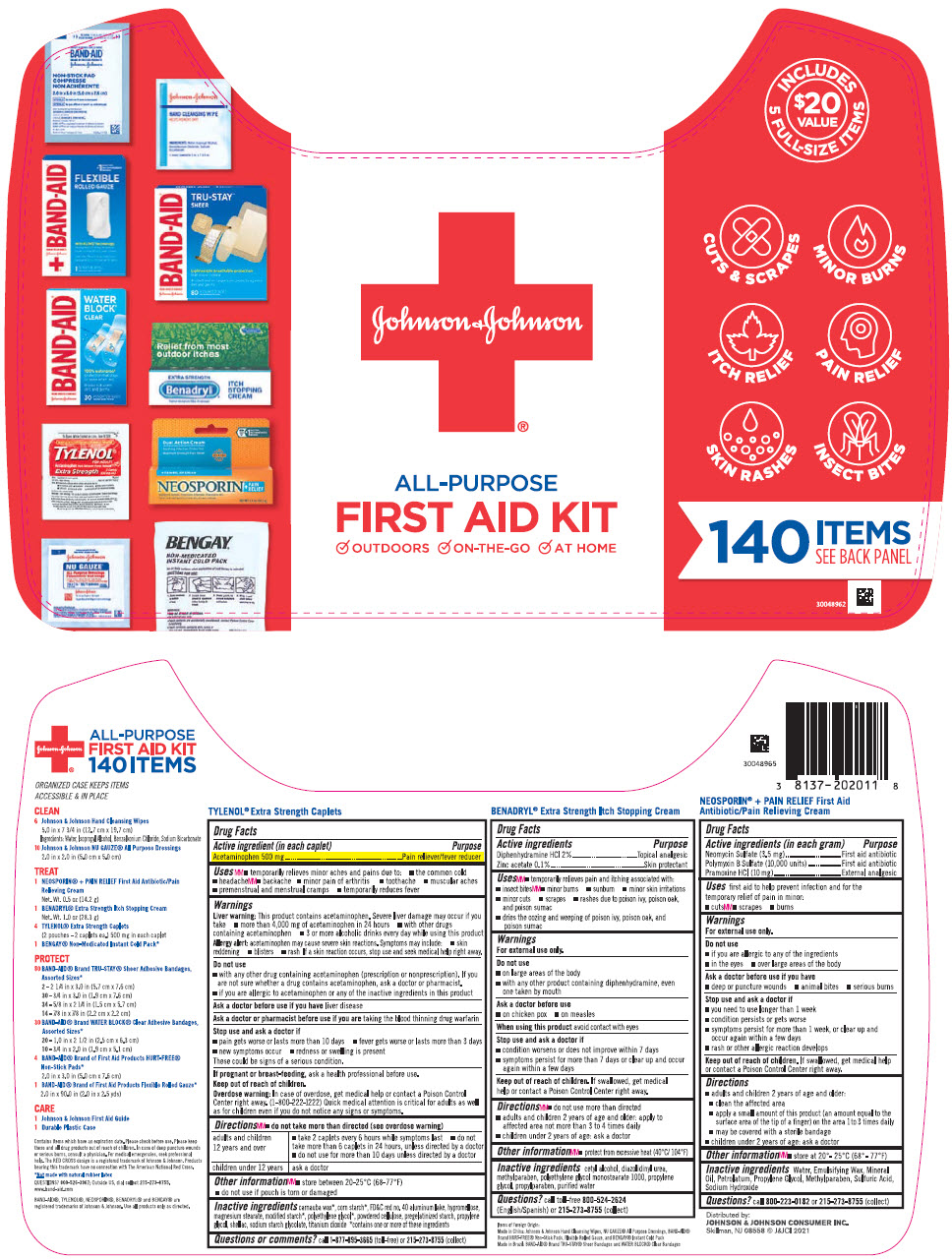 DRUG LABEL: Johnson and Johnson All Purpose First Aid Kit
NDC: 69968-0711 | Form: KIT | Route: ORAL
Manufacturer: Kenvue Brands LLC
Category: otc | Type: HUMAN OTC DRUG LABEL
Date: 20251106

ACTIVE INGREDIENTS: ACETAMINOPHEN 500 mg/1 1; DIPHENHYDRAMINE HYDROCHLORIDE 20 mg/1 g; ZINC ACETATE 1 mg/1 g; NEOMYCIN SULFATE 3.5 mg/1 g; POLYMYXIN B SULFATE 10000 [USP'U]/1 g; PRAMOXINE HYDROCHLORIDE 10 mg/1 g
INACTIVE INGREDIENTS: CARNAUBA WAX; STARCH, CORN; FD&C RED NO. 40; ALUMINUM OXIDE; HYPROMELLOSE, UNSPECIFIED; MAGNESIUM STEARATE; POLYETHYLENE GLYCOL, UNSPECIFIED; POWDERED CELLULOSE; PROPYLENE GLYCOL; SHELLAC; SODIUM STARCH GLYCOLATE TYPE A POTATO; TITANIUM DIOXIDE; CETYL ALCOHOL; DIAZOLIDINYL UREA; METHYLPARABEN; PROPYLENE GLYCOL; PROPYLPARABEN; WATER; WATER; MINERAL OIL; PETROLATUM; PROPYLENE GLYCOL; METHYLPARABEN; SULFURIC ACID; SODIUM HYDROXIDE

Johnson and Johnson All Purpose First Aid Kit

Drug Facts

Active ingredient (in each caplet)

Acetaminophen 500 mg

Purpose

Pain reliever/fever reducer

Uses

- temporarily relieves minor aches and pains due to:
  - the common cold
  - headache
  - backache
  - minor pain of arthritis
  - toothache
  - muscular aches
  - premenstrual and menstrual cramps
- temporarily reduces fever

Warnings

Liver warning

This product contains acetaminophen. Severe liver damage may occur if you take

- more than 4,000 mg of acetaminophen in 24 hours
- with other drugs containing acetaminophen
- 3 or more alcoholic drinks every day while using this product

Allergy alert: acetaminophen may cause severe skin reactions. Symptoms may include:

- skin reddening
- blisters
- rash

If a skin reaction occurs, stop use and seek medical help right away.

Do not use

- with any other drug containing acetaminophen (prescription or nonprescription). If you are not sure whether a drug contains acetaminophen, ask a doctor or pharmacist.
- if you are allergic to acetaminophen or any of the inactive ingredients in this product

Ask a doctor before use if you have liver disease

Ask a doctor or pharmacist before use if you are taking the blood thinning drug warfarin

Stop use and ask a doctor if

- pain gets worse or lasts more than 10 days
- fever gets worse or lasts more than 3 days
- new symptoms occur
- redness or swelling is present

These could be signs of a serious condition.

PREGNANCY OR BREAST FEEDING

If pregnant or breast-feeding, ask a health professional before use.

Keep out of reach of children.

Overdose warning

In case of overdose, get medical help or contact a Poison Control Center right away. (1-800-222-1222) Quick medical attention is critical for adults as well as for children even if you do not notice any signs or symptoms.

Directions

- do not take more than directed (see overdose warning)

adults and children 12 years and over | - take 2 caplets every 6 hours while symptoms last - do not take more than 6 caplets in 24 hours, unless directed by a doctor - do not use for more than 10 days unless directed by a doctor
children under 12 years | ask a doctor

Other information

- store between 20-25°C (68-77°F)
- do not use if pouch is torn or damaged

Inactive ingredients

carnauba wax [contains one or more of these ingredients] , corn starch , FD&C red no. 40 aluminum lake, hypromellose, magnesium stearate, modified starch , polyethylene glycol , powdered cellulose, pregelatinized starch, propylene glycol, shellac, sodium starch glycolate, titanium dioxide

Questions or comments?

call 1-877-895-3665 (toll-free) or 215-273-8755 (collect)

Drug Facts

ACTIVE INGREDIENT

Active ingredients | Purpose
Diphenhydramine hydrochloride 2% | Topical analgesic
Zinc acetate 0.1% | Skin protectant

Uses

- temporarily relieves pain and itching associated with:
  - insect bites
  - minor burns
  - sunburn
  - minor skin irritations
  - minor cuts
  - scrapes
  - rashes due to poison ivy, poison oak, and poison sumac
- dries the oozing and weeping of poison ivy, poison oak, and poison sumac

Warnings

For external use only

Do not use

- on large areas of the body
- with any other product containing diphenhydramine, even one taken by mouth

Ask a doctor before use

- on chicken pox
- on measles

When using this product avoid contact with eyes

Stop use and ask a doctor if

- condition worsens or does not improve within 7 days
- symptoms persist for more than 7 days or clear up and occur again within a few days

Keep out of reach of children. If swallowed, get medical help or contact a Poison Control Center right away.

Directions

- do not use more than directed
- adults and children 2 years of age and older: apply to affected area not more than 3 to 4 times daily
- children under 2 years of age: ask a doctor

Other information

- protect from excessive heat (40°C/104°F)

Inactive ingredients

cetyl alcohol, diazolidinyl urea, methylparaben, polyethylene glycol monostearate 1000, propylene glycol, propylparaben, purified water

Questions?

call toll-free 800-524-2624 (English/Spanish) or 215-273-8755 (collect)

Drug Facts

ACTIVE INGREDIENT

Active ingredients (in each gram) | Purpose
Neomycin Sulfate (3.5 mg) | First aid antibiotic
Polymyxin B Sulfate (10,000 units) | First aid antibiotic
Pramoxine HCl (10 mg) | External analgesic

Uses

first aid to help prevent infection and for the temporary relief of pain in minor:

- cuts
- scrapes
- burns

Warnings

For external use only.

Do not use

- if you are allergic to any of the ingredients
- in the eyes
- over large areas of the body

Ask a doctor before use if you have

- deep or puncture wounds
- animal bites
- serious burns

Stop use and ask a doctor if

- you need to use longer than 1 week
- condition persists or gets worse
- symptoms persist for more than 1 week, or clear up and occur again within a few days
- rash or other allergic reaction develops

Keep out of reach of children.

If swallowed, get medical help or contact a Poison Control Centre right away.

Directions

- adults and children 2 years of age and older:
  - clean the affected area
  - apply a small amount of this product (an amount equal to the surface area of the tip of a finger) on the area 1 to 3 times daily
  - may be covered with a sterile bandage
- children under 2 years of age: ask a doctor

Other information

- store at 20° to 25°C (68° to 77°F)

Inactive ingredients

Water, Emulsifying Wax, Mineral Oil, Petrolatum, Propylene Glycol, Methylparaben, Sulfuric acid, Sodium Hydroxide

Questions?

call 800-223-0182 or 215-273-8755 (collect)

Distributed by:
JOHNSON & JOHNSON CONSUMER INC.
Skillman, NJ 08558

PRINCIPAL DISPLAY PANEL - Kit Package Label

Johnson & Johnson®

ALL-PURPOSE

FIRST AID KIT

OUTDOORS
ON-THE-GO
AT HOME

INCLUDES
$20
VALUE
5 FULL-SIZE ITEMS

CUTS & SCRAPES
MINOR BURNS

ITCH RELIEF
PAIN RELIEF

SKIN RASHES
INSECT BITES

140 ITEMS

SEE BACK PANEL